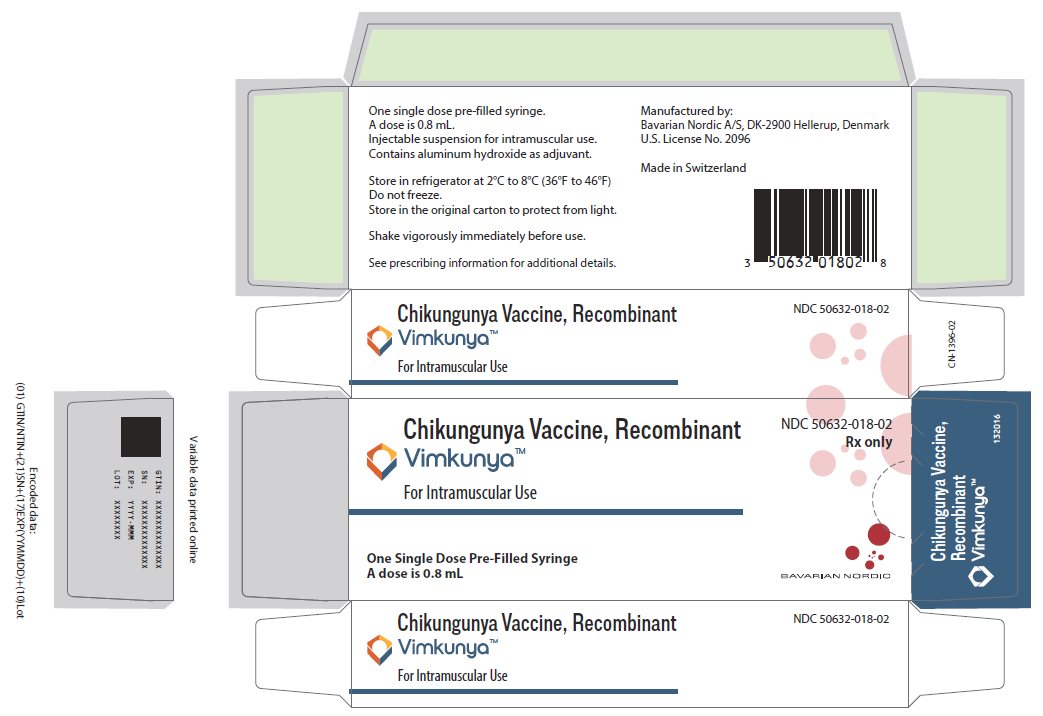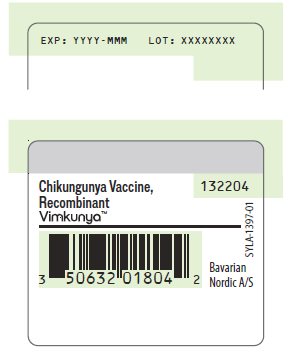 DRUG LABEL: VIMKUNYA
NDC: 50632-018 | Form: INJECTION, SUSPENSION
Manufacturer: Bavarian Nordic A/S
Category: other | Type: VACCINE LABEL
Date: 20250218

ACTIVE INGREDIENTS: CHIKUNGUNYA VIRUS SENEGAL STRAIN 37997 CAPSID PROTEIN 10 ug/0.8 mL; CHIKUNGUNYA VIRUS SENEGAL STRAIN 37997 ENVELOPE PROTEIN E1 15 ug/0.8 mL; CHIKUNGUNYA VIRUS SENEGAL STRAIN 37997 ENVELOPE PROTEIN E2 15 ug/0.8 mL
INACTIVE INGREDIENTS: ALUMINUM HYDROXIDE; SUCROSE; SODIUM CITRATE, UNSPECIFIED FORM; DIBASIC POTASSIUM PHOSPHATE; MONOBASIC POTASSIUM PHOSPHATE; WATER

HIGHLIGHTS OF PRESCRIBING INFORMATION

These highlights do not include all the information needed to use VIMKUNYATM safely and effectively. See full prescribing information for VIMKUNYATM.
VIMKUNYA™ (Chikungunya Vaccine, Recombinant) injectable suspension, for intramuscular use
Initial U.S. Approval: 2025

1 INDICATIONS AND USAGE

VIMKUNYA is a vaccine indicated for the prevention of disease caused by chikungunya virus in individuals 12 years of age and older. (1)

The indication is approved under accelerated approval based on anti-chikungunya virus neutralizing antibody levels. Continued approval for this indication may be contingent upon verification and description of clinical benefit in a confirmatory trial.

2 DOSAGE AND ADMINISTRATION

For intramuscular use. (2)

Administer VIMKUNYA as a single 0.8 mL dose. (2.1)

3 DOSAGE FORMS AND STRENGTHS

VIMKUNYA is an injectable suspension. A single dose is 0.8 mL. (3)

4 CONTRAINDICATIONS

Do not administer VIMKUNYA to anyone with a history of a severe allergic reaction (e.g., anaphylaxis) to any component of VIMKUNYA. (4)

5 WARNINGS AND PRECAUTIONS

- Appropriate medical treatment must be immediately available to manage potential anaphylactic reactions following administration of VIMKUNYA. (5.1)
- Immunocompromised individuals, including individuals receiving immunosuppressive therapy, may have a diminished immune response to VIMKUNYA. (5.2)
- Syncope (fainting) may occur in association with administration of injectable vaccines including VIMKUNYA. Procedures should be in place to avoid injury from fainting. (5.3)

6 ADVERSE REACTIONS

- The most commonly reported solicited adverse reactions (>10%) in individuals 12 through 64 years of age were injection site pain (23.7%), fatigue (19.9%), headache (18.0%), and myalgia (17.6%). (6.1)
- The most commonly reported solicited adverse reactions (>5%) in individuals 65 years of age and older were injection site pain (5.4%), myalgia (6.3%), and fatigue (6.3%). (6.1)

To report SUSPECTED ADVERSE REACTIONS, contact Bavarian Nordic Inc. at 1-833-365-9596 or drug.safety@bavarian-nordic.com or VAERS at 1-800-822-7967 or www.vaers.hhs.gov.

FULL PRESCRIBING INFORMATION

1 INDICATIONS AND USAGE

VIMKUNYA is a vaccine indicated for the prevention of disease caused by chikungunya virus (CHIKV) in individuals 12 years of age and older.

This indication is approved under accelerated approval based on anti-CHIKV neutralizing antibody levels [see Clinical Studies (14)]. Continued approval for this indication may be contingent upon verification and description of clinical benefit in a confirmatory trial.

2 DOSAGE AND ADMINISTRATION

For intramuscular use.

2.1 Dose and Schedule

Administer VIMKUNYA as a single 0.8 mL dose.

2.2 Preparation

Shake the pre-filled syringe vigorously immediately before use to form a homogeneous suspension. After shaking, the suspension should be a white, cloudy liquid.

Parenteral drug products should be inspected visually for particulate matter and discoloration prior to administration, whenever solution and container permit. Discard if either condition is present.

2.3 Administration

Administer VIMKUNYA intramuscularly.

VIMKUNYA may be held at room temperature (up to 25°C or 77°F) for up to 2 hours after removal from refrigerator. Discard the vaccine if not used within 2 hours after removal from refrigerator.

3 DOSAGE FORMS AND STRENGTHS

VIMKUNYA is an injectable suspension. A single dose is 0.8 mL.

4 CONTRAINDICATIONS

Do not administer VIMKUNYA to individuals with a history of a severe allergic reaction (e.g., anaphylaxis) to any component of the vaccine [see Description (11)].

5 WARNINGS AND PRECAUTIONS

5.1 Management of Allergic Reactions

Appropriate medical treatment must be immediately available to manage potential anaphylactic reactions following administration of VIMKUNYA.

5.2 Altered Immunocompetence

Immunocompromised individuals, including individuals receiving immunosuppressive therapy, may have a diminished immune response to VIMKUNYA.

5.3 Syncope

Syncope (fainting) may occur in association with administration of injectable vaccines including VIMKUNYA. Procedures should be in place to avoid injury from fainting.

6 ADVERSE REACTIONS

In participants 12 through 64 years of age who received VIMKUNYA, the most common solicited local adverse reaction (>10%) was injection site pain (23.7%). The most common solicited systemic adverse reactions (>10%) were fatigue (19.9%), headache (18.0%), and myalgia (17.6%).

In participants 65 years of age and older who received VIMKUNYA, the most common solicited local adverse reaction (>5%) was injection site pain (5.4%). The most common solicited systemic adverse reactions (>5%) were myalgia (6.3%) and fatigue (6.3%).

6.1 Clinical Trials Experience

Because clinical trials are conducted under widely varying conditions, adverse reaction rates observed in the clinical trials of a vaccine cannot be directly compared to rates in the clinical trials of another vaccine and may not reflect the rates observed in practice.

The safety of VIMKUNYA was evaluated in two clinical trials [Study 1 (NCT05072080) and Study 2 (NCT05349617)], both conducted in the United States, in which a total of 3,667 participants 12 years of age and older received a single dose of VIMKUNYA or placebo [formulation buffer containing 218 mM sucrose, 10 mM potassium phosphate, 25 mM sodium citrate, pH 7.0 (see Description (11)].

Study 1 was a multicenter, randomized, placebo-controlled, double-blinded trial. Individuals aged 12 through 64 years were randomized in a 6:1 ratio, stratified by age stratum (12-17, 18-45, and 46-64 years of age), to receive a single dose of VIMKUNYA (n=2,794) or placebo (n=464).

Among the overall 3,258 participants randomized in Study 1, the median age was 38 years [with 254 (8%) participants 12 through 17 years of age, 1906 (58%) participants 18 through 45 years of age, and 1098 (34%) participants 46 through 64 years of age]; 51.2% were female; 73.2% were White, 19.1% Black or African American, 2.9% Asian, 1.0% American Indian or Alaska Native, 0.3% Native Hawaiian or Pacific Islander, 2.6% multiple racial groups; and 17.7% were of Hispanic or Latino ethnicity.

Study 2 was a multicenter, randomized, placebo-controlled, double-blinded trial. Individuals aged 65 years and older were randomized in a 1:1 ratio, stratified by age stratum (65-74 and ≥75 years of age), to receive a single dose of VIMKUNYA (n=206) or placebo (n=207).

Among the overall 413 participants enrolled in Study 2, the median age was 70 years, and 58.6% were female; 83.3% were White, 11.9% Black or African American, 1.2% Asian, 0.5% American Indian or Alaska Native, 2.2% multiple racial groups; and 44.3% were of Hispanic or Latino ethnicity.

In Studies 1 and 2, solicited adverse reactions were collected via electronic diary from the vaccination day through 7 days post-vaccination (an 8-day period). Unsolicited adverse events were monitored for 28 days post-vaccination. Serious adverse events were monitored through 6 months post-vaccination. New onset or worsening arthralgia that was medically attended was monitored through 6 months post-vaccination.

Solicited Adverse Reactions

The percentage of participants in Study 1 reporting solicited local (injection site) and systemic adverse reactions is shown in Table 1. In Study 1, the median day of onset was Day 1 for local reactions (Day 1 was the day of vaccination) and Day 2 for systemic reactions following administration of VIMKUNYA. Local and systemic adverse reactions resolved with a median duration of 1 day.

Table 1. Percentages of Participants with Solicited Local and Systemic Adverse Reactions Through 7 Days After Vaccination (Study 1a, 12 through 64 years of age)
Adverse Reaction | VIMKUNYA N=2790 % | Placebo N=464 %
Solicited Local (Injection Site) Adverse Reactionsb
Pain (any)c,f | 23.7 | 10.7
Pain (severe) | 0.1 | 0
Redness/Erythema (≥25 mm)f | 0.5 | 0
Redness/Erythema (>100 mm) | <0.1 | 0
Swelling (≥25 mm)f | 0.4 | 0
Solicited Systemic Adverse Reactionsb
Fatigue (any)d,f | 19.9 | 17.0
Fatigue (severe) | 0.7 | 0.2
Headache (any)c,h | 18.0 | 16.6
Headache (severe) | 0.3 | 0.4
Myalgia/Muscle Pain (any)d,f | 17.6 | 9.6
Myalgia/Muscle Pain (severe) | 0.4 | 0.4
Chills (any)d,f | 8.6 | 3.3
Chills (severe) | 0.1 | 0
Arthralgia/Joint Pain (any)d,f | 7.7 | 7.2
Arthralgia/Joint Pain (severe) | 0.3 | 0.2
Nausea (any)e,f | 7.5 | 6.6
Nausea (severe) | 0.4 | 0
Fever (≥38.0°C or ≥100.4°F)g | 0.9 | 0.2
Fever (≥39.0°C or ≥102.1°F) | 0.2 | 0
Note: Solicited adverse reactions were collected from the vaccination day through 7 days post-vaccination (an 8-day period). Percentages are based on the number of participants in the Study 1 safety population with at least one diary observation for a given symptom for a given day.
a NCT05072080
b Severity=mild, moderate, severe intensity. Absence of rows for severe reactions indicates that no reactions of this severity were reported in either group.
c Defined as mild (no interference with activity), moderate (repeated use of non-narcotic pain reliever >24 hours or interference with activity), severe (any use of narcotic pain reliever or prevents daily activity).
d Defined as mild (no interference with activity), moderate (some interference with activity), severe (prevents daily activity).
e Defined as mild (no interference with activity or 1 – 2 episodes/24 hours), moderate (some interference with activity or >2 episodes/24 hours), severe (prevents daily activity, requires outpatient intravenous hydration).
f The denominator for injection site pain, redness, swelling, arthralgia, chills, fatigue, myalgia, and nausea is 2,764 for VIMKUNYA and 458 for placebo.
g The denominator for fever is 2,760 for VIMKUNYA and 457 for placebo.
h The denominator for headache is 2,765 for VIMKUNYA and 458 for placebo.

In Study 1, solicited adverse reactions were reported by 94 (44.1%) participants12 through 17 years of age, 676 (41.8%) participants 18 through 45 years of age, and 289 (31.0%) participants 46 through 64 years of age in the VIMKUNYA group.

The percentage of participants in Study 2 reporting solicited local and systemic adverse reactions is shown in Table 2. In Study 2, the median day of onset was Day 2 for both local and systemic reactions (Day 1 was the day of vaccination) following administration of VIMKUNYA. Local adverse reactions resolved with a median duration of 1 day and systemic adverse reactions resolved with a median duration of 2 days.

Table 2. Percentages of Participants with Solicited Local and Systemic Adverse Reactions Through 7 Days After Vaccination (Study 2a, 65 years of age and greater)
Adverse Reaction | VIMKUNYA N=205 % | Placebo N=200 %
Solicited Local (Injection Site) Adverse Reactionsb
Pain (any)c | 5.4 | 1.5
Redness/Erythema (≥25 mm) | 0 | 0.5
Swelling (≥25 mm) | 0 | 0
Solicited Systemic Adverse Reactionsb
Myalgia/Muscle Pain (any)d | 6.3 | 6.5
Fatigue (any)d | 6.3 | 6.0
Fatigue (severe) | 0.5 | 0
Headache (any)c | 4.4 | 7.5
Headache (severe) | 0.5 | 0
Arthralgia/Joint Pain (any)d | 2.9 | 4.0
Chills (any)d | 2.9 | 3.0
Nausea (any)e | 2.9 | 1.5
Fever (≥38.0°C or ≥100.4°F) | 0 | 1.0
Note: Solicited adverse reactions were collected from the vaccination day through 7 days post-vaccination (an 8-day period). N=Number of participants in the Study 2 safety population with at least one diary observation for a given symptom for a given day.
a NCT05349617
b Severity=mild, moderate, severe intensity. Absence of rows for severe reactions indicates that no reactions of this severity were reported in either group.
c Defined as mild (no interference with activity), moderate (repeated use of non-narcotic pain reliever > 24 hours or interference with activity), severe (any use of narcotic pain reliever or prevents daily activity).
d Defined as mild (no interference with activity), moderate (some interference with activity), severe (prevents daily activity).
e Defined as mild (no interference with activity or 1 – 2 episodes/24 hours), moderate (some interference with activity or >2 episodes/24 hours), severe (prevents daily activity, requires outpatient intravenous hydration).

Unsolicited Adverse Events

In Study 1, unsolicited adverse events that occurred within 28 days following vaccination were reported in 15.5% of 2,790 participants who received VIMKUNYA and 12.7% of 464 participants who received placebo. There was one report of severe dehydration considered related to VIMKUNYA.

In Study 2, unsolicited adverse events that occurred within 28 days following vaccination were reported in 12.6% of 206 participants who received VIMKUNYA and 15.5% of 207 participants who received placebo. There were no severe unsolicited adverse events considered related to VIMKUNYA.

Medically Attended New Onset or Worsening Arthralgia

In Study 1, 3 (0.1%) participants in the VIMKUNYA group (n=2,790) and 1 (0.2%) participant in the placebo group (n=464) reported new onset or worsening arthralgia that was medically attended and considered possibly or probably related to VIMKUNYA (beginning 2, 14 and 84 days post-vaccination, respectively) or possibly related to placebo (beginning 1 day post-vaccination); none of these reactions were reported as serious or severe (defined as those that prevented daily activity and/or required medical intervention).

In Study 2, there were no participants in the VIMKUNYA or placebo groups with new onset or worsening arthralgia that was medically attended and considered at least possibly related to the study intervention.

8 USE IN SPECIFIC POPULATIONS

8.1 Pregnancy

Pregnancy Exposure Registry

There is a pregnancy exposure registry that monitors pregnancy outcomes in women exposed to VIMKUNYA during pregnancy. Women who receive VIMKUNYA during pregnancy are encouraged to contact, or have their healthcare provider contact, 1-888-230-2491 to enroll in or obtain information about the registry.

Risk Summary

All pregnancies have a risk of birth defect, loss, or other adverse outcomes. In the US general population, the estimated background risk of major birth defects and miscarriage in clinically recognized pregnancies is 2% to 4% and 15% to 20%, respectively.

There are no clinical studies of VIMKUNYA in pregnant women. Data on VIMKUNYA administered to pregnant women are insufficient to inform vaccine-associated risks in pregnancy.

A developmental toxicity study was performed in female rabbits, administered the equivalent of a single human dose of VIMKUNYA on 5 occasions, twice prior to mating, twice during gestation and once during lactation. In this study, postnatal survival of the kits was reduced; there were no adverse effects on other postnatal development parameters. There were no adverse effects on female fertility; and there was no evidence of harm to the fetus due to the vaccine. A developmental toxicity study was performed in female rats administered the equivalent of a single human dose of VIMKUNYA on 5 occasions, twice prior to mating, twice during gestation and once during lactation. In this study there were no adverse effects on postnatal survival and on other postnatal development parameters. There were no adverse effects on female fertility. [see Data].

Clinical Considerations

Disease-associated maternal and/or embryo/fetal risk

Vertical transmission of wild-type CHIKV to neonates from pregnant women with viremia at delivery is common and can cause severe, potentially fatal CHIKV disease in neonates, with neurologic (e.g., encephalopathy, intracranial hemorrhage) and myocardial manifestations.^1

Data

Animal Data

In a pre- and postnatal developmental study with an embryo-fetal development toxicity phase performed in female rabbits, a full human dose (0.8 mL) of VIMKUNYA was administered by intramuscular injection on five occasions: 28 and 14 days prior to start of cohabitation, on Gestation Days 7 and 21 and on Lactation Day 7. Among kits born in the control group, 69% of the kits [95% confidence interval (CI) (57.8%, 80.1%)] survived compared to the 42% of kits [95% CI (31.5%, 52.8%)] born to vaccinated mothers (the historical control data showed a range for postnatal survival from 47.6% to 91.4% with a mean of 71%, from 18 studies); other postnatal development parameters were not affected. There were no adverse effects on female fertility; and there was no evidence of harm to the fetus due to the vaccine.

In a pre- and postnatal developmental study performed in female rats, a full human dose (0.8 mL) of VIMKUNYA was administered by intramuscular injection on five occasions: 28 and 14 days prior to start of cohabitation, on Gestation Days 7 and 21 and on Lactation Day 7. No vaccine related adverse effects on female fertility or postnatal development were observed.

8.2 Lactation

Risk Summary

Human data are not available to assess the impact of VIMKUNYA on milk production, its presence in breast milk, or its effects on the breastfed child. The developmental and health benefits of breastfeeding should be considered along with the mother’s clinical need for VIMKUNYA and any potential adverse effects on the breastfed child from VIMKUNYA or from the underlying maternal condition. For preventive vaccines, the underlying condition is susceptibility to disease prevented by the vaccine.

8.4 Pediatric Use

The safety and effectiveness of VIMKUNYA in individuals 12 through 17 years of age are based on data from this age group and data from adults [see Adverse Reactions (6.1) and Clinical Studies (14)].

The safety and effectiveness of VIMKUNYA in individuals younger than 12 years of age have not been established.

8.5 Geriatric Use

In Study 2, the 206 individuals who received VIMKUNYA were 65 years of age and older; and among these, 47 individuals (22.8%) were 75 years of age and older. The incidence of solicited adverse reactions in individuals 65 years of age and older was generally lower than that observed in individuals less than 65 years of age [see Adverse Reactions (6.1)]. The seroresponse rate in individuals 65 years of age and older was lower than that observed in individuals less than 65 years of age [see Clinical Studies (14)].

11 DESCRIPTION

VIMKUNYA, Chikungunya Vaccine, Recombinant, is a sterile injectable suspension for intramuscular use. VIMKUNYA contains purified virus-like particles (VLPs) consisting of CHIKV capsid protein (C) and envelope proteins E1 and E2, derived from CHIKV Senegal strain 37997. The VLPs are produced by transfecting an expression plasmid that encodes for the CHIKV structural polyprotein C-E3-E2-6K-E1 in HEK293 (a continuous line of human embryonic kidney cells) in media containing amino acids, vitamins, and minerals. The VLPs containing C, E1 and E2, are harvested from the media and then purified by a series of chemical and physical methods. After sterile filtration, the purified VLPs are mixed with formulation buffer and adsorbed on aluminum hydroxide [Al(OH)3] as adjuvant.

Each 0.8-mL dose contains approximately 40 mcg of CHIKV VLPs. Each dose also contains 867 mcg Al(OH)3 (approximately 300 mcg aluminum), 59.7 mg sucrose, 5.9 mg sodium citrate dihydrate, 0.9 mg potassium phosphate dibasic, 0.4 mg potassium phosphate monobasic, and water for injection. Each dose may contain residual amounts of HEK293 cell protein (less than 400 ng/dose), HEK293 cell DNA (less than 10 ng/dose), poloxamer 188 (less than 2850 mcg/dose), polyethyleneimine (less than 4 mcg/dose), valproic acid (less than 12.8 mcg/dose), Benzonase (less than 1.6 ng/dose), and plasmid DNA (less than 3.6 ng/dose), from the manufacturing process.

VIMKUNYA does not contain a preservative or antibiotics.

The syringe stoppers and caps are not made with natural rubber latex.

12 CLINICAL PHARMACOLOGY

12.1 Mechanism of Action

The exact mechanism of protection has not been determined. VIMKUNYA elicits CHIKV-specific immune responses.

13 NONCLINICAL TOXICOLOGY

13.1 Carcinogenesis, Mutagenesis, Impairment of Fertility

VIMKUNYA has not been evaluated for the potential to cause carcinogenicity, mutagenic potential, or for impairment of male fertility in animals.

13.2 Animal Toxicology and/or Pharmacology

A passive transfer study was performed in non-human primates (NHPs) using human anti-CHIKV immune sera collected from two Phase 2 studies (NCT03483961 and NCT03992872), from participants who received a single dose of a vaccine formulation containing the same CHIKV VLP used in VIMKUNYA. Sera obtained on Day 22 after vaccination were pooled to generate a serum pool with a NT80 titer of 2470, as determined by a CHIKV luciferase neutralization assay. In the passive transfer study, 20 CHIKV-naïve cynomolgus macaques (M. fascicularis) were administered human anti-CHIKV immune sera at four dose levels (2.4, 1.2, 0.6 and 0.3 mL/kg) and 6 CHIKV-naïve cynomolgus macaques were administered non-immune control sera by intravenous injection. One day after the transfers, serum samples were obtained from the macaques to determine pre-challenge anti-CHIKV neutralizing antibody titers by the CHIKV luciferase neutralization assay. On the same day following sera collection, animals were challenged via the subcutaneous route with 100,000 Plaque Forming Units of wild-type CHIKV strain La Réunion 2006-OPY1, corresponding to 1000 times the 50% animal infectious dose. Animal monitoring included assessment of wild-type CHIKV-induced viremia by plaque assay and RT-qPCR through 10 days after challenge. For those NHPs that received anti-CHIKV sera, no infectious virus was detected in the blood, and the amounts of CHIKV RNA in the blood were reduced in a dose-dependent manner compared with NHPs who received non-immune human sera. Data from the NHP study were analyzed by logistic regression and a NT80 titer of ≥100 was determined to be reasonably likely to predict clinical benefit in the Phase 3 studies.

14 CLINICAL STUDIES

The immunogenicity of VIMKUNYA was assessed in Studies 1 and 2 [see Adverse Reactions (6.1)]. In both studies, the assessment of effectiveness was based on seroresponse rate at Day 22 and the serum neutralizing antibody (SNA) geometric mean titer (GMT) at Day 22. The seroresponse rate and GMT 21 days after a single dose of VIMKUNYA in Study 1 is presented in Table 3.

Table 3. GMTs and Seroresponse Rates 21 Days Post-vaccination as Determined by Anti-CHIKV Human SNA Assay in Study 1 (12 through 64 years of age)
GMTa VIMKUNYA N=2559 (95% CI) | GMTa Placebo N=424 (95% CI) | GMT Ratioa,e, VIMKUNYA over Placebo (95% CI)
1597.0 (1504.1, 1695.6) | 7.9 (7.0, 8.8) | 203.3 (181.1, 228.2)
Seroresponse Rateb,d VIMKUNYA N=2559 % (95% CI) | Seroresponse Rateb,d Placebo N=424 % (95% CI) | Seroresponse Rate Differencec,f VIMKUNYA minus Placebo (95% CI)
97.8 (97.2, 98.3) | 1.2 (0.5, 2.7) | 96.6 (95.0, 97.5)
CHIKV=Chikungunya virus; CI=confidence interval; GMT=geometric mean titer; SNA=serum neutralizing antibody.
N=Exposed participants who had at least one post-injection anti-CHIKV SNA result, no measurable anti-CHIKV SNA at Day 1, an evaluable Day 22 serum sample result within window (Day 19 through Day 27, inclusive), and no important protocol deviation deemed exclusionary.
a GMT estimates, together with their 95% CIs, are derived from an ANOVA model that includes site and vaccine group as fixed effects, assuming normality of the log titers. GMTs ratios and 95% CIs are derived from the same model.
b 95% CIs of seroresponse rates are based on the Wilson method.
c 95% CIs of seroresponse rate differences are based on the Newcombe hybrid score method.
d Seroresponse rate is defined as the percentage of participants who have achieved an anti-CHIKV neutralizing antibody titer ≥100 measured by luciferase-based CHIKV neutralization assay. The neutralizing antibody titer is expressed as a serum dilution achieving 80% neutralization (NT80). This threshold was derived from a non-human primate model [see Nonclinical Toxicology (13.2)].
e Success criterion: lower bound of the 95% CI for GMT ratio > 1.
f Success criterion: lower bound of the 95% CI for seroresponse rate difference ≥70%.

The seroresponse rate and GMT 21 days after a single dose of VIMKUNYA in Study 2 is presented in Table 4.

Table 4. GMTs and Seroresponse Rates 21 Days Post-vaccination as Determined by Anti-CHIKV Human SNA Assay in Study 2 (65 years of age and older)
GMTa VIMKUNYA N=189 (95% CI) | GMTa Placebo N=183 (95% CI) | GMT Ratioa,e, VIMKUNYA over Placebo (95% CI)
721.0 (582.3, 892.7) | 8.08 (6.5, 10.0) | 89.2 (68.4, 116.4)
Seroresponse Rateb,d VIMKUNYA N=189 % (95% CI) | Seroresponse Rateb,d Placebo N=183 % (95% CI) | Seroresponse Rate Differencec,f VIMKUNYA minus Placebo (95% CI)
87.3 (81.8, 91.3) | 1.1 (0.3, 3.9) | 86.2 (80.0, 90.3)
CHIKV=Chikungunya virus; CI=confidence interval; GMT=geometric mean titer; SNA=serum neutralizing antibody.
N=Exposed participants who had at least one post-injection anti-CHIKV SNA result, no measurable anti-CHIKV SNA at Day 1, an evaluable Day 22 serum sample result within window (Day 19 through Day 27, inclusive), and no important protocol deviation deemed exclusionary.
a GMT estimates, together with their 95% CIs, are derived from an ANOVA model that includes site and vaccine group as fixed effects, assuming normality of the log titers. GMTs ratios and 95% CIs are derived from the same model.
b 95% CIs of seroresponse rates are based on the Wilson method.
c 95% CIs of seroresponse rate differences are based on the Newcombe hybrid score method.
d Seroresponse rate is defined as the percentage of participants who have achieved an anti-CHIKV neutralizing antibody titer ≥100 measured by luciferase-based CHIKV neutralization assay. The neutralizing antibody titer is expressed as a serum dilution achieving 80% neutralization (NT80). This threshold was derived from a non-human primate model [see Nonclinical Toxicology (13.2)].
e Success criterion: lower bound of the 95% CI for GMT ratio > 1.
f Success criterion: lower bound of the 95% CI for seroresponse rate difference ≥70%.

The seroresponse rate at 183 days post-vaccination in Study 1 was 85.5% among VIMKUNYA participants and 1.5% among placebo participants (seroresponse rate difference: 84.0% [95% CI: 81.7, 85.6]). The seroresponse rate at 183 days post-vaccination in Study 2 was 75.5% among VIMKUNYA participants and 1.2% among placebo participants (seroresponse rate difference: 74.4% [95% CI: 67.1, 80.1]).

15 REFERENCES

1. Gérardin P, Barau G, Michault A, Bintner M, Randrianaivo H, Choker G, et al. Multidisciplinary prospective study of mother-to-child chikungunya virus infections on the island of La Réunion. PLoS Med. 2008;5(3):0413–2.

16 HOW SUPPLIED/STORAGE AND HANDLING

VIMKUNYA is supplied in a carton (NDC 50632-018-02) containing one single dose pre-filled syringe (NDC 50632-018-04) (packaged without needles).

Store VIMKUNYA in a refrigerator at 2°C to 8°C (36°F to 46°F). Store in the original carton to protect from light. DO NOT FREEZE.

VIMKUNYA may be held at room temperature (up to 25°C or 77°F) for up to 2 hours after removal from refrigerator. Discard the vaccine if not used within 2 hours after removal from refrigerator.

17 PATIENT COUNSELING INFORMATION

Inform the vaccine recipient:

- about the potential benefits and risks associated with vaccination with VIMKUNYA.
- that vaccination with VIMKUNYA may not protect all vaccine recipients and that personal precautions should be taken to reduce exposure to mosquito bites (e.g., adequate clothing, use of repellents, mosquito nets).

Instruct the vaccine recipient to report any adverse reactions to their health care provider, the vaccine manufacturer at 1-833-365-9596 (or online at drug.safety@bavarian-nordic.com), or through the Vaccine Adverse Event Reporting System (VAERS) at 1-800-822-7967 (or online at www.vaers.hhs.gov).

Encourage women exposed to VIMKUNYA around the time of conception or during pregnancy to enroll in the pregnancy registry by calling 1-888-230-2491 or by visiting bnpregnancyregistry.com [See Use in Specific Populations (8.1)].

______________________________________________________________________________________________

Manufactured by:
Bavarian Nordic A/S
Philip Heymans Alle 3
2900 Hellerup, Denmark

U.S. License No. 2096

BAVARIAN NORDIC

PACKAGE/LABEL PRINCIPAL DISPLAY PANEL

NDC 50632-018-02
Rx only

Chikungunya Vaccine, Recombinant
VimkunyaTM
For Intramuscular Use

One Single Dose Pre-Filled Syringe
A dose is 0.8 mL

BAVARIAN NORDIC

PACKAGE/LABEL PRINCIPAL DISPLAY PANEL

EXP: YYYY-MM LOT: XXXXXXXX

Chikungunya Vaccine, Recombinant ^132204
VimkunyaTM

Bavarian Nordic A/S

SYLA-1397-01